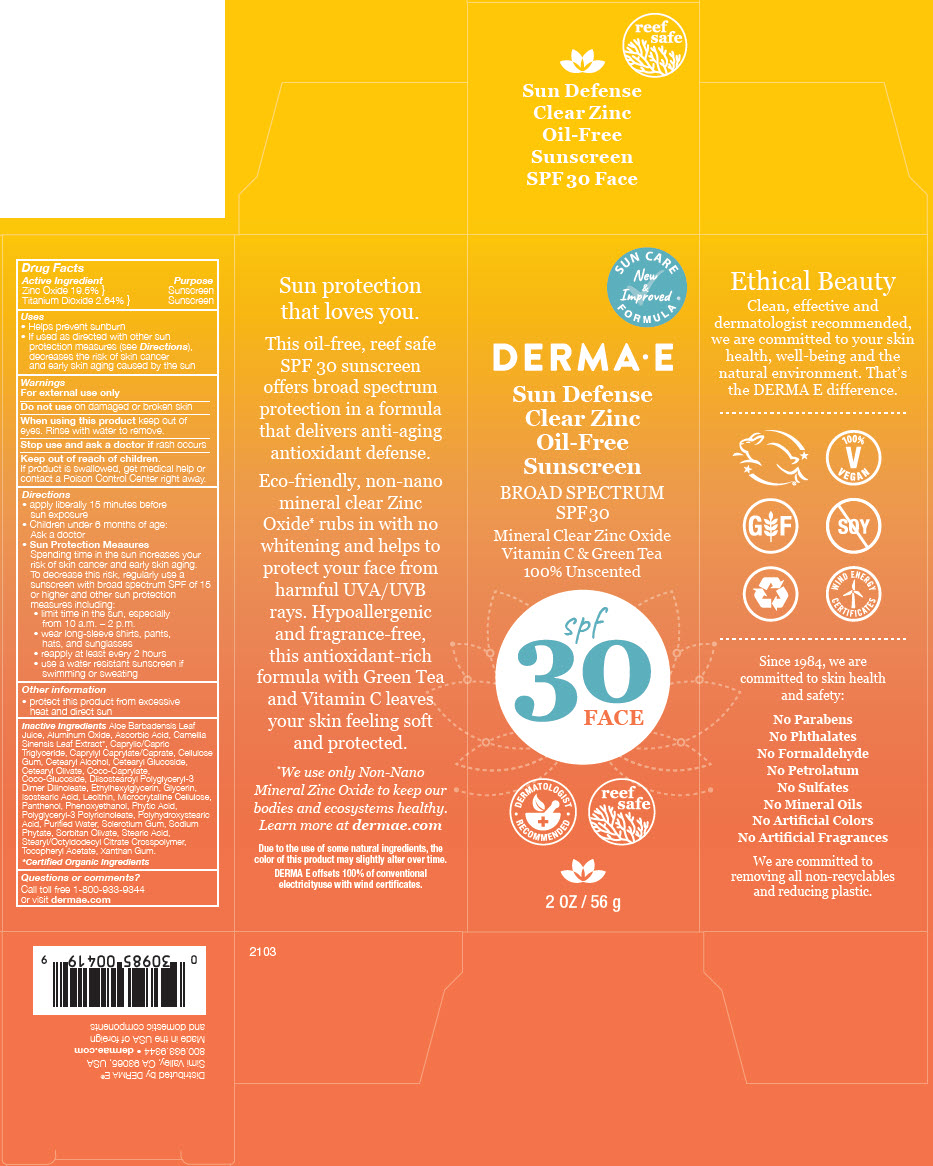 DRUG LABEL: Derma E Sun Defense Face
NDC: 54108-0419 | Form: LOTION
Manufacturer: derma e
Category: otc | Type: HUMAN OTC DRUG LABEL
Date: 20240717

ACTIVE INGREDIENTS: ZINC OXIDE 195 mg/1 g; TITANIUM DIOXIDE 26.4 mg/1 g
INACTIVE INGREDIENTS: ALOE VERA LEAF; ALUMINUM OXIDE; ASCORBIC ACID; GREEN TEA LEAF; MEDIUM-CHAIN TRIGLYCERIDES; CAPRYLYL CAPRYLATE/CAPRATE; CARBOXYMETHYLCELLULOSE; CETOSTEARYL ALCOHOL; CETEARYL GLUCOSIDE; CETEARYL OLIVATE; COCO-GLUCOSIDE; DIISOSTEAROYL POLYGLYCERYL-3 DIMER DILINOLEATE; ETHYLHEXYLGLYCERIN; GLYCERIN; ISOSTEARIC ACID; LECITHIN, SUNFLOWER; MICROCRYSTALLINE CELLULOSE; PANTHENOL; PHENOXYETHANOL; FYTIC ACID; POLYGLYCERYL-3 PENTARICINOLEATE; POLYHYDROXYSTEARIC ACID (2300 MW); WATER; BETASIZOFIRAN; PHYTATE SODIUM; SORBITAN OLIVATE; STEARIC ACID; STEARYL/OCTYLDODECYL CITRATE CROSSPOLYMER; .ALPHA.-TOCOPHEROL ACETATE; XANTHAN GUM

Derma E Sun Defense Face
SPF 30

Drug Facts

ACTIVE INGREDIENT

Active Ingredient | Purpose
Zinc Oxide 19.5% } | Sunscreen
Titanium Dioxide 2.64% } | Sunscreen

Uses

- Helps prevent sunburn
- If used as directed with other sun protection measures (see Directions), decreases the risk of skin cancer and early skin aging caused by the sun

Warnings

For external use only

Do not use on damaged or broken skin

When using this product keep out of eyes. Rinse with water to remove.

Stop use and ask a doctor if rash occurs

Keep out of reach of children.

If product is swallowed, get medical help or contact a Poison Control Center right away.

Directions

- apply liberally 15 minutes before sun exposure
- Children under 6 months of age: Ask a doctor
- Sun Protection Measures
  Spending time in the sun increases your risk of skin cancer and early skin aging. To decrease this risk, regularly use a sunscreen with broad spectrum SPF of 15 or higher and other sun protection measures including:
  - limit time in the sun, especially from 10 a.m. – 2 p.m.
  - wear long-sleeve shirts, pants, hats, and sunglasses
  - reapply at least every 2 hours
  - use a water resistant sunscreen if swimming or sweating

Other information

- protect this product from excessive heat and direct sun

Inactive Ingredients

Aloe Barbadensis Leaf Juice, Aluminum Oxide, Ascorbic Acid, Camellia Sinensis Leaf Extract [Certified Organic Ingredients] , Caprylic/Capric Triglyceride, Caprylyl Caprylate/Caprate, Cellulose Gum, Cetearyl Alcohol, Cetearyl Glucoside, Cetearyl Olivate, Coco-Caprylate, Coco-Glucoside, Diisostearoyl Polyglyceryl-3 Dimer Dilinoleate, Ethylhexylglycerin, Glycerin, Isostearic Acid, Lecithin, Microcrytalline Cellulose, Panthenol, Phenoxyethanol, Phytic Acid, Polyglyceryl-3 Polyricinoleate, Polyhydroxystearic Acid, Purified Water, Sclerotium Gum, Sodium Phytate, Sorbitan Olivate, Stearic Acid, Stearyl/Octyldodecyl Citrate Crosspolymer, Tocopheryl Acetate, Xanthan Gum.

Questions or comments?

Call toll free 1-800-933-9344 or visit dermae.com

Distributed by DERMA E®
Simi Valley, CA 93065, USA

PRINCIPAL DISPLAY PANEL - 56 g Tube Box

SUN CARE
New
&
Improved
FORMULA

DERMA • E

Sun Defense
Clear Zinc
Oil-Free
Sunscreen

BROAD SPECTRUM
SPF 30

Mineral Clear Zinc Oxide
Vitamin C & Green Tea
100% Unscented

spf
30
FACE

• DERMATOLOGIST
RECOMMENDED •

reef
safe

2 OZ / 56 g